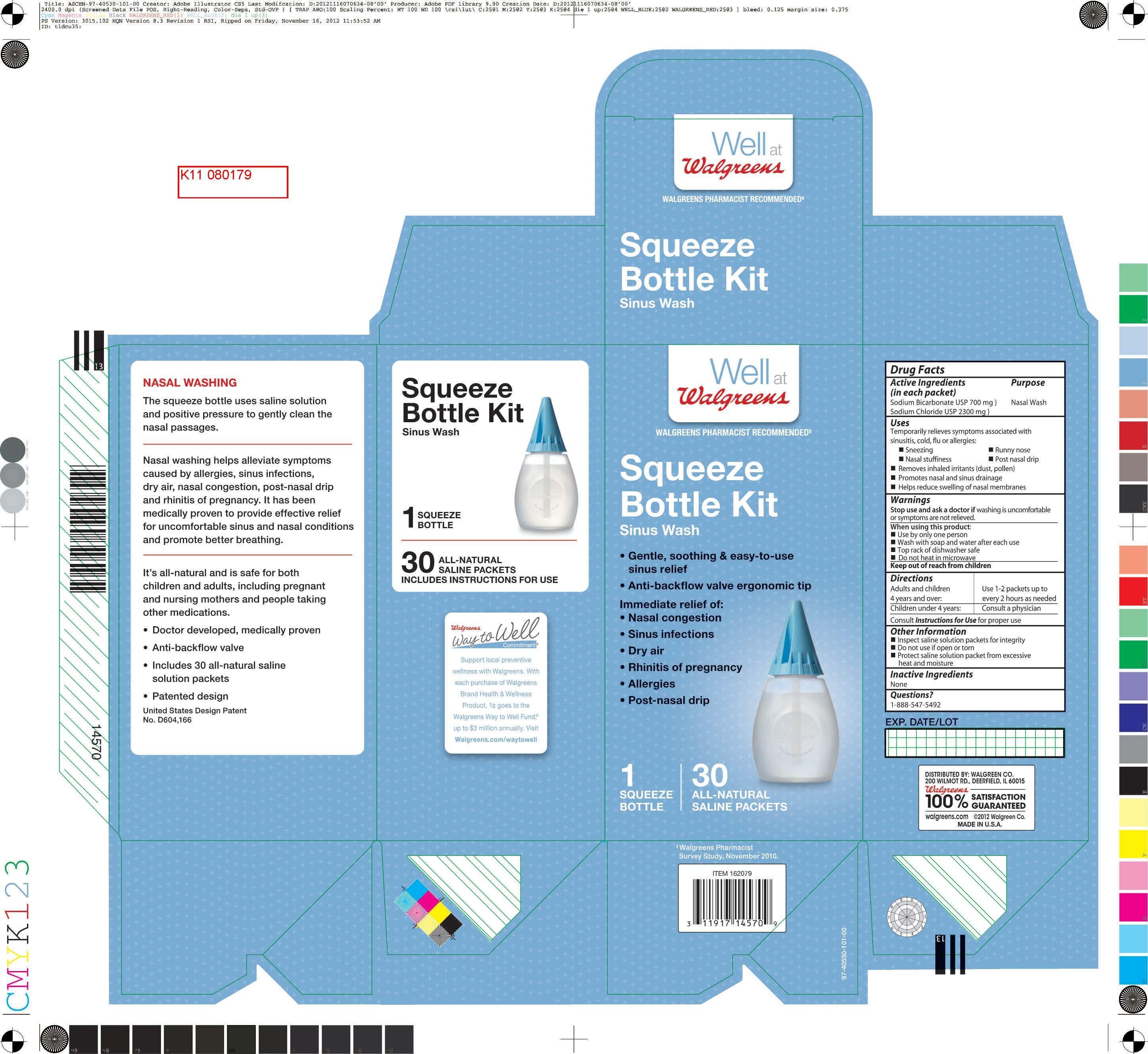 DRUG LABEL: Well at Walgreens
                
                
                
NDC: 0363-0405 | Form: KIT | Route: NASAL
Manufacturer: Walgreen Company
Category: otc | Type: HUMAN OTC DRUG LABEL
Date: 20150530

ACTIVE INGREDIENTS: SODIUM CHLORIDE 2300 mg/3000 mg; SODIUM BICARBONATE 700 mg/3000 mg

Drug Facts

Purpose

Nasal Wash

Uses

Temporarily relieves symptoms associated with

sinusitis, cold, flu or allergies

-Sneezing

-Nasal Stuffiness

-Runny nose

-Post nasal drip

Removes inhaled irritants (dust, pollen)

Removes nasal and sinus drainage

Helps reduce swelling of nasal membranes

Moisturizes dry nasal passages

Keep out of reach of children

Warnings

Stop use and ask a doctor if washing is uncomfortable

or symptoms are not relieved.

Do not use unfiltered tap water. see instructions inside box for proper water sources

Directions

Adults and children 4 years and over: Use 1-2 packets per 8 fl oz (240 mL) up to every two hours as needed.

Children under 4 years: Consult a physician

See enclosed instruction sheet for complete directions and proper use.

Instructions for Use of the Squeeze Bottle:

Directions and Dosage: Read through entire section before using for the first time.

1. Remove the cap from the squeeze bottle.

2. Pour the pre-mixed saline dry into the Squeeze Bottle. First-time users

should start with 1 packet of the saline dry ingredients. As you become more accustomed to the system, work up to using 2 full packets,

Additional packets may be purchased from your nearest pharmacy.

3. Fill the bottle with proper water* leaving approximately 1/2 inch of air at the top of the bottle.

This makes 1 cup (8 oz) of solution.

4. Tighten the cap on the bottle securely, place one finger over the tip of the cap and and gently shake the bottle until

the dry ingredients have completely dissolved.

5. Lean over the sink with your head bent so you are looking directly directly into the basin. Place the tip of the cap up to the right nostril and gently insert the tip

so that it forms a comfortable seal. Aim the tip at the back of your head, not at the top of your head.

6. Squeeze the bottle gently so that the solution enters the right nostril. Do not inhale or "snort" the solution into your nose - breathe through your mouth.

7. In a few moments the solution will begin to drain out of the left nostril. Continue to squeeze the bottle gently until you have

used approximately half of the solution.

8. Remove the tip of the bottle from your nostril, then exhale through both nostrils to clear them of

excess mucus and solution. Gently blow your nose into a tissue.

9. Repeat the procedure on the left nostril with the remaining solution.

10. A small amount of the solution will remain in the bottom of the bottle. Discard the remaining solution.

11. Thoroughly rinse the bottle after each use with water that has been distilled, sterilized,

filtered or previously boiled and leave the bottle open to air dry completely. The Squeeze Bottle is

top-rack dishwasher safe.

Active ingredients

(in each packet)

Sodium Bicarbonate USP (700 mg)

Sodium Chloride USP (2300 mg)

Inactive Ingredients

None